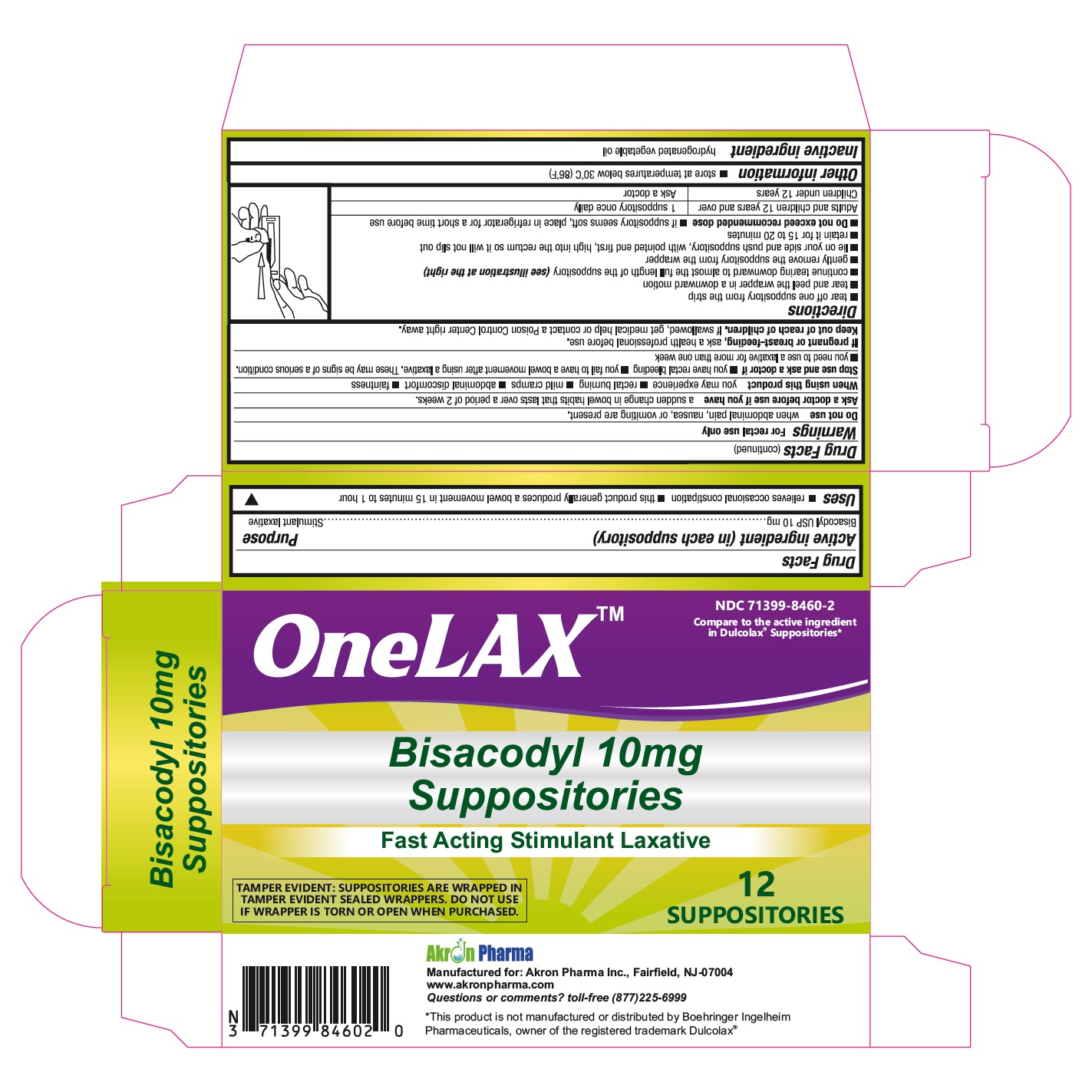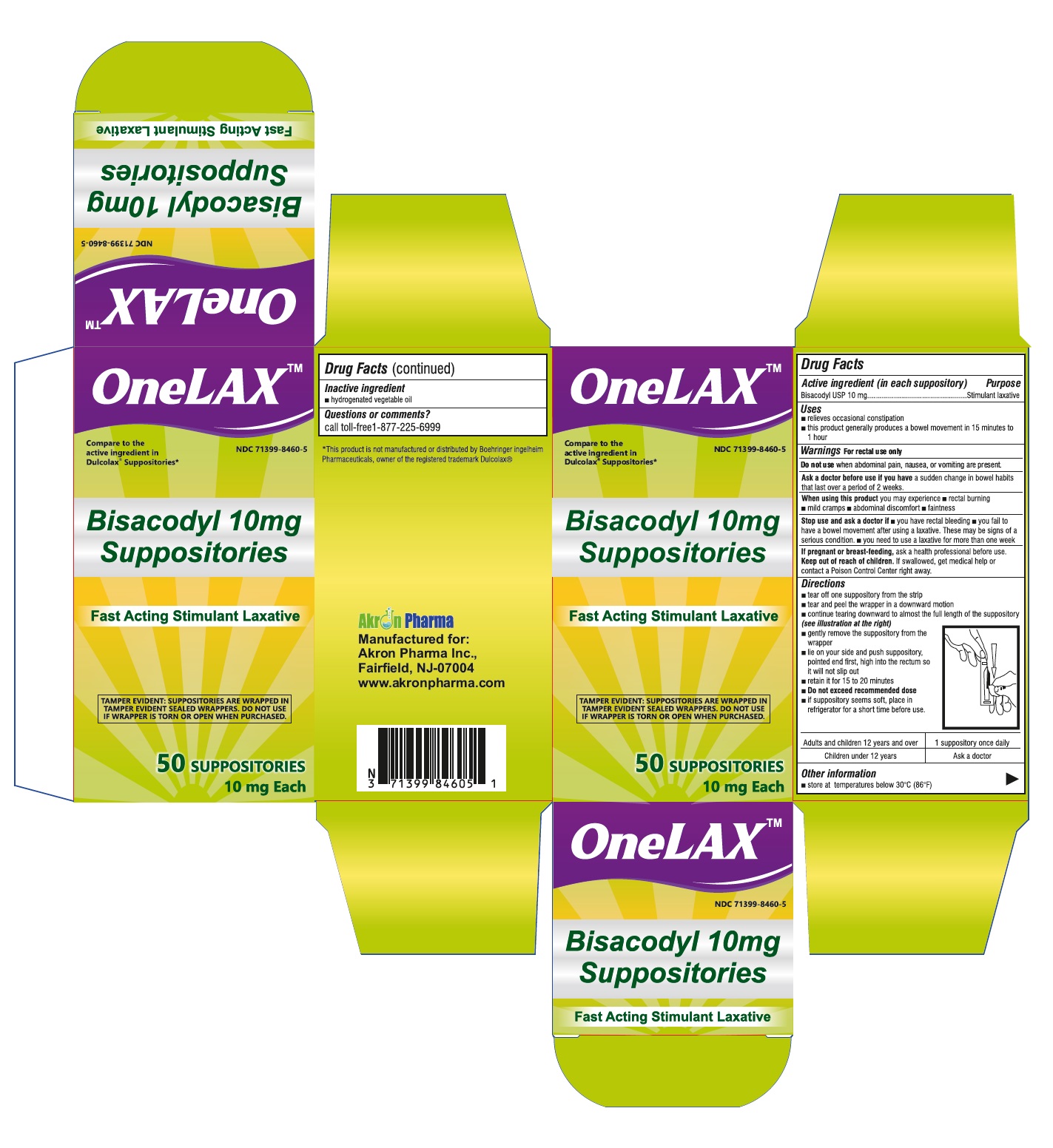 DRUG LABEL: OneLAX
NDC: 71399-8460 | Form: SUPPOSITORY
Manufacturer: AKRON PHARMA INC
Category: otc | Type: HUMAN OTC DRUG LABEL
Date: 20251103

ACTIVE INGREDIENTS: BISACODYL 10 mg/1 1
INACTIVE INGREDIENTS: FAT, HARD

OneLAX
BISACODYL 10 mg Suppositories
Fast Acting Stimulant Laxative

Active Ingredients (per suppository)

Bisacodyl USP, 10 mg

Purpose

Laxative

Keep out of reach of children. If swallowed, get medical help or contact a Poison Control Center right away.

Uses

- for relief of occasional constipation
- this product usually produces bowel movement in 1/4 to 1 hour

Warnings

For rectal use only.

Do not use laxative products

- when abdominal pain, nausea or vomiting are present
- for a period longer than one week

Ask a doctor before use if you have

noticed a sudden change in bowel habits that persist over a period of 2 weeks

When using this product

it may cause abdominal discomfort, faintness, rectal burning and mild cramps

Stop use and ask a doctor if

rectal bleeding occurs, or you fail to have a bowel movement after using a laxative. This may indicate a serious condition.

If pregnant or breast-feeding

ask a health professional before use.

Directions

- adults and children 12 years of age and older
- detach one suppository from the strip
- remove from wrapper before inserting into the rectum
- the rectal suppository dose is one suppository per day or as directed by a doctor
- children under 12 years of age consult a doctor

Other information

store below 30° C (86° F)

Inactive ingredient

hydrogenated vegetable oil

Manufactured for:
Akron Pharma Inc.,
Fairfield, NJ-07004
www.akronpharma.com